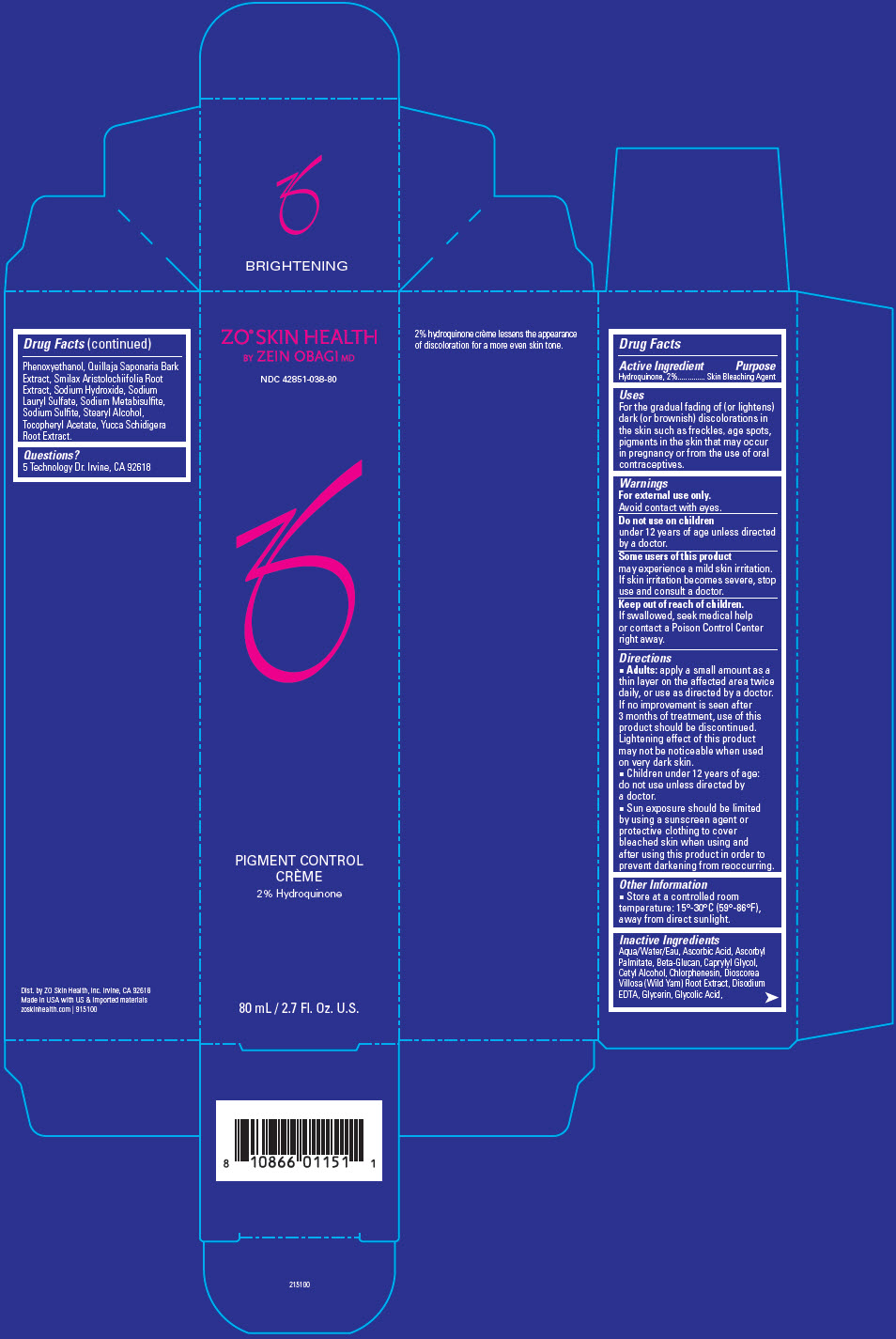 DRUG LABEL: ZO Skin Health Pigment Control Creme Hydroquinone
NDC: 42851-038 | Form: LOTION
Manufacturer: ZO Skin Health, Inc.
Category: otc | Type: HUMAN OTC DRUG LABEL
Date: 20220425

ACTIVE INGREDIENTS: HYDROQUINONE 20 mg/1 mL
INACTIVE INGREDIENTS: WATER; ASCORBIC ACID; ASCORBYL PALMITATE; CAPRYLYL GLYCOL; CETYL ALCOHOL; CHLORPHENESIN; DIOSCOREA VILLOSA TUBER; EDETATE DISODIUM ANHYDROUS; GLYCERIN; GLYCOLIC ACID; PHENOXYETHANOL; QUILLAJA SAPONARIA BARK; SMILAX ARISTOLOCHIIFOLIA ROOT; SODIUM HYDROXIDE; SODIUM LAURYL SULFATE; SODIUM METABISULFITE; SODIUM SULFITE; STEARYL ALCOHOL; .ALPHA.-TOCOPHEROL ACETATE; YUCCA SCHIDIGERA ROOT

ZO® Skin Health Pigment Control Creme 2% Hydroquinone
National Drug Code 42851-038-80

Drug Facts

Active Ingredient

Hydroquinone, 2%

Purpose

Skin Bleaching Agent

Uses

For the gradual fading of (or lightens) dark (or brownish) discolorations in the skin such as freckles, age spots, pigments in the skin that may occur in pregnancy or from the use of oral contraceptives.

Warnings

For external use only.

Avoid contact with eyes.

Do not use on children under 12 years of age unless directed by a doctor.

STOP USE

Some users of this product may experience a mild skin irritation. If skin irritation becomes severe, stop use and consult a doctor.

Keep out of reach of children.

If swallowed, seek medical help or contact a Poison Control Center right away.

Directions

- Adults: apply a small amount as a thin layer on the affected area twice daily, or use as directed by a doctor. If no improvement is seen after 3 months of treatment, use of this product should be discontinued. Lightening effect of this product may not be noticeable when used on very dark skin.
- Children under 12 years of age: do not use unless directed by a doctor.
- Sun exposure should be limited by using a sunscreen agent or protective clothing to cover bleached skin when using and after using this product in order to prevent darkening from reoccurring.

Other Information

- Store at a controlled room temperature: 15°-30°C (59°-86°F), away from direct sunlight.

Inactive Ingredients

Aqua/Water/Eau, Ascorbic Acid, Ascorbyl Palmitate, Beta-Glucan, Caprylyl Glycol, Cetyl Alcohol, Chlorphenesin, Dioscorea Villosa (Wild Yam) Root Extract, Disodium EDTA, Glycerin, Glycolic Acid, Phenoxyethanol, Quillaja Saponaria Bark Extract, Smilax Aristolochiifolia Root Extract, Sodium Hydroxide, Sodium Lauryl Sulfate, Sodium Metabisulfite, Sodium Sulfite, Stearyl Alcohol, Tocopheryl Acetate, Yucca Schidigera Root Extract.

Questions?

5 Technology Dr. Irvine, CA 92618

Dist. by ZO Skin Health, Inc. Irvine, CA 92618

PRINCIPAL DISPLAY PANEL - 80 mL Bottle Carton

ZO® SKIN HEALTH
BY ZEIN OBAGI MD

NDC 42851-038-80

PIGMENT CONTROL
CRÈME
2% Hydroquinone

80 mL / 2.7 Fl. Oz. U.S.